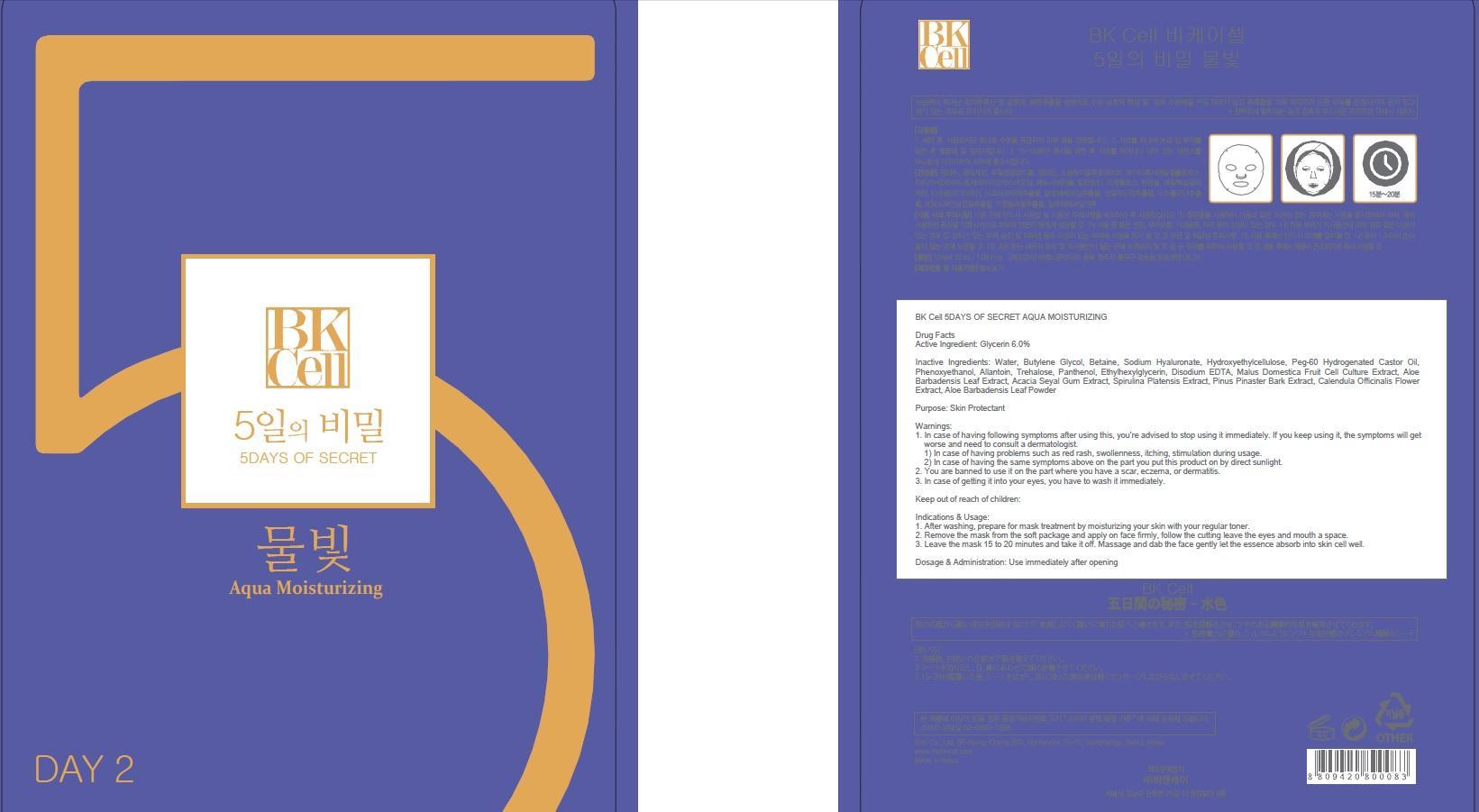 DRUG LABEL: BK Cell 5DAYS OF SECRET AQUA MOISTURIZING
NDC: 69946-020 | Form: PATCH
Manufacturer: BNK CO., LTD.
Category: otc | Type: HUMAN OTC DRUG LABEL
Date: 20150715

ACTIVE INGREDIENTS: Glycerin 1.92 mg/32 mL
INACTIVE INGREDIENTS: Water; Butylene Glycol

ACTIVE INGREDIENT

Active Ingredient: Glycerin 6.0%

INACTIVE INGREDIENT

Inactive Ingredients: Water, Butylene Glycol, Betaine, Sodium Hyaluronate, Hydroxyethylcellulose, Peg-60 Hydrogenated Castor Oil, Phenoxyethanol, Allantoin, Trehalose, Panthenol, Ethylhexylglycerin, Disodium EDTA, Malus Domestica Fruit Cell Culture Extract, Aloe Barbadensis Leaf Extract, Acacia Seyal Gum Extract, Spirulina Platensis Extract, Pinus Pinaster Bark Extract, Calendula Officinalis Flower Extract, Aloe Barbadensis Leaf Powder

PURPOSE

Purpose: Skin Protectant

WARNINGS

Warnings: 1. In case of having following symptoms after using this, you're advised to stop using it immediately. If you keep using it, the symptoms will get worse and need to consult a dermatologist. 1) In case of having problems such as red rash, swollenness, itching, stimulation during usage. 2) In case of having the same symptoms above on the part you put this product on by direct sunlight. 2. You are banned to use it on the part where you have a scar, eczema, or dermatitis. 3. In case of getting it into your eyes, you have to wash it immediately.

KEEP OUT OF REACH OF CHILDREN

Keep out of reach of babies and children

INDICATIONS & USAGE

Indications & Usage: 1. After washing, prepare for mask treatment by moisturizing your skin with your regular toner. 2. Remove the mask from the soft package and apply on face firmly, follow the cutting leave the eyes and mouth a space. 3. Leave the mask 15 to 20 minutes and take it off. Massage and dab the face gently let the essence absorb into skin cell well.

DOSAGE & ADMINISTRATION

Dosage & Administration: Use immediately after opening